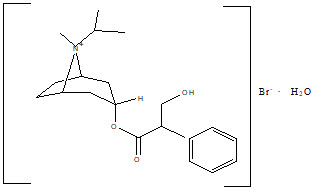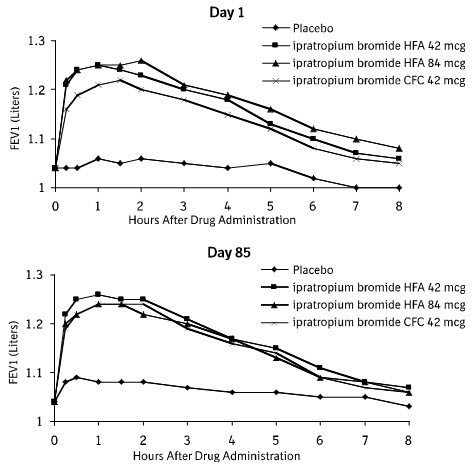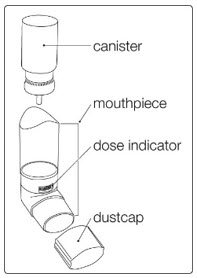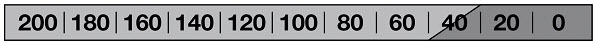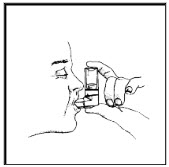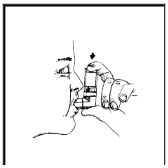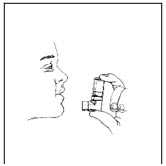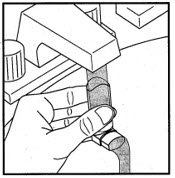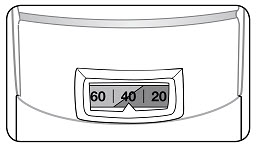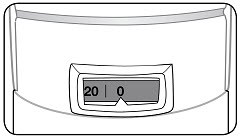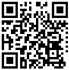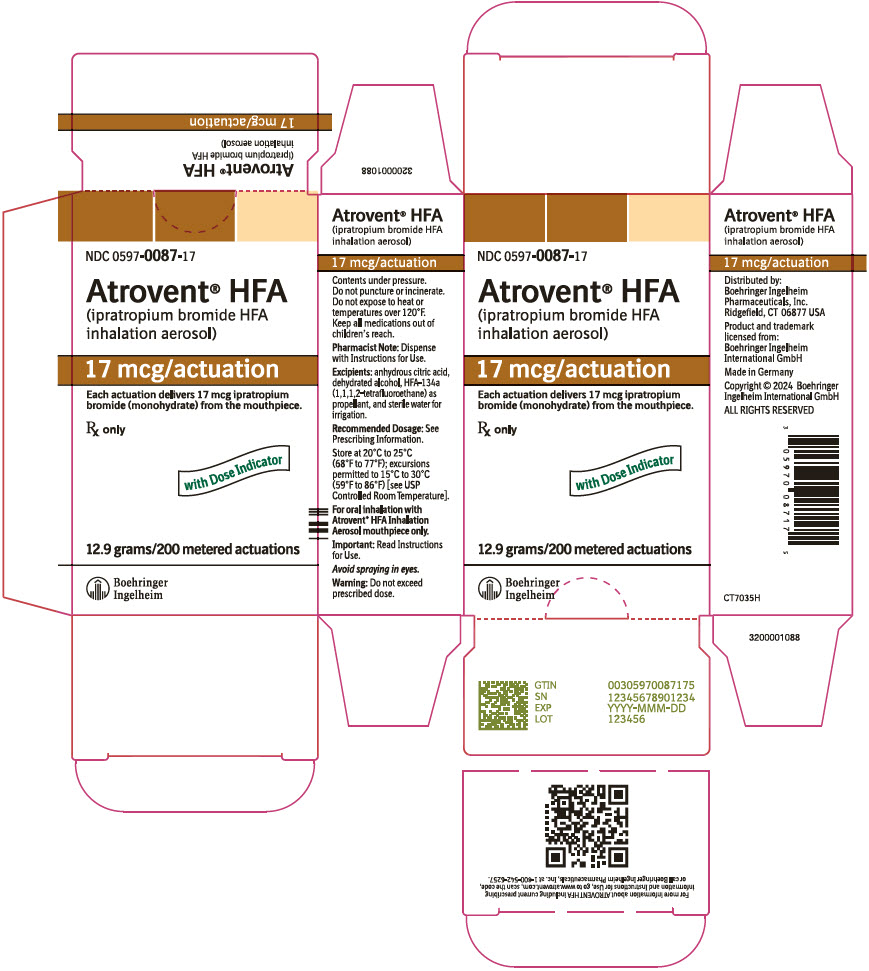 DRUG LABEL: Atrovent
NDC: 0597-0087 | Form: AEROSOL, METERED
Manufacturer: Boehringer Ingelheim Pharmaceuticals, Inc.
Category: prescription | Type: HUMAN PRESCRIPTION DRUG LABEL
Date: 20251105

ACTIVE INGREDIENTS: IPRATROPIUM BROMIDE 17 ug/1 1

HIGHLIGHTS OF PRESCRIBING INFORMATION

These highlights do not include all the information needed to use ATROVENT HFA safely and effectively. See full prescribing information for ATROVENT HFA.
ATROVENT® HFA (ipratropium bromide HFA inhalation aerosol), for oral inhalation use
Initial U.S. Approval: 2004

1 INDICATIONS AND USAGE

ATROVENT HFA is an anticholinergic indicated for the maintenance treatment of bronchospasm associated with chronic obstructive pulmonary disease (COPD), including chronic bronchitis and emphysema (1)

2 DOSAGE AND ADMINISTRATION

For oral inhalation only

- Two inhalations four times a day, not to exceed 12 inhalations in 24 hours (2)

3 DOSAGE FORMS AND STRENGTHS

- Inhalation Aerosol: Each actuation of ATROVENT HFA Inhalation Aerosol delivers 17 mcg of ipratropium bromide (monohydrate) from the mouthpiece (3)
- Supplied in a 12.9 g canister containing 200 actuations (3)

4 CONTRAINDICATIONS

- Hypersensitivity to ipratropium bromide or other ATROVENT HFA components (4)
- Hypersensitivity to atropine or any of its derivatives (4)

5 WARNINGS AND PRECAUTIONS

- Not indicated for the initial treatment of acute episodes of bronchospasm where rescue therapy is required for rapid response (5.1)
- Hypersensitivity reactions including anaphylaxis: Discontinue ATROVENT HFA at once and consider alternative treatments (5.2)
- Paradoxical bronchospasm: Discontinue ATROVENT HFA and consider other treatments if paradoxical bronchospasm occurs (5.3)
- Ocular effects: Use with caution in patients with narrow-angle glaucoma and instruct patients to consult a physician immediately if signs or symptoms of narrow-angle glaucoma develop (5.4)
- Urinary retention: Use with caution in patients with prostatic hyperplasia or bladder-neck obstruction and instruct patients to consult a physician immediately if signs or symptoms of urinary retention develop (5.5)

6 ADVERSE REACTIONS

Most common adverse reactions (>5% incidence in the 12-week placebo-controlled trials) were bronchitis, COPD exacerbation, dyspnea, and headache (6.1)

To report SUSPECTED ADVERSE REACTIONS, contact Boehringer Ingelheim Pharmaceuticals, Inc. at 1-800-542-6257 or FDA at 1-800-FDA-1088 or www.fda.gov/medwatch.

7 DRUG INTERACTIONS

Anticholinergics: May interact additively with concomitantly used anticholinergic medications. Avoid administration of ATROVENT HFA with other anticholinergic-containing drugs (7.1)

FULL PRESCRIBING INFORMATION

1 INDICATIONS AND USAGE

ATROVENT HFA Inhalation Aerosol is indicated as a bronchodilator for maintenance treatment of bronchospasm associated with chronic obstructive pulmonary disease (COPD), including chronic bronchitis and emphysema.

2 DOSAGE AND ADMINISTRATION

The usual starting dosage of ATROVENT HFA is two inhalations four times a day. Patients may take additional inhalations as required; however, the total number of inhalations should not exceed 12 in 24 hours.

ATROVENT HFA is a solution aerosol that does not require shaking. However, as with any other metered-dose inhaler, some coordination is required between actuating the canister and inhaling the medication.

Patients should "prime" or actuate ATROVENT HFA before using for the first time by releasing 2 test sprays into the air away from the face. In cases where the inhaler has not been used for more than 3 days, prime the inhaler again by releasing 2 test sprays into the air away from the face. Patients should avoid spraying ATROVENT HFA into their eyes.

Each inhaler provides sufficient medication for 200 actuations. The inhaler should be discarded after the labeled number of actuations has been used. The amount of medication in each actuation cannot be assured after this point, even though the canister is not completely empty.

Patients should be instructed on the proper use of their inhaler [see Patient Counseling Information (17)].

3 DOSAGE FORMS AND STRENGTHS

ATROVENT HFA is an inhalation aerosol supplied in a pressurized stainless steel canister as a metered-dose inhaler with a white mouthpiece that has a clear, colorless sleeve and a green protective cap. Each pressurized metered-dose aerosol unit for oral inhalation contains a 12.9 g solution of ipratropium bromide (monohydrate) that provides sufficient medication for 200 actuations. After priming, each actuation of the inhaler delivers 21 mcg of ipratropium bromide (monohydrate) from the valve and delivers 17 mcg of ipratropium bromide (monohydrate) from the mouthpiece.

4 CONTRAINDICATIONS

ATROVENT HFA is contraindicated in the following conditions [see Warnings and Precautions (5.2)].

- Hypersensitivity to ipratropium bromide or other ATROVENT HFA components
- Hypersensitivity to atropine or any of its derivatives

5 WARNINGS AND PRECAUTIONS

5.1 Use for Maintenance Treatment Only

ATROVENT HFA is a bronchodilator for the maintenance treatment of bronchospasm associated with COPD and is not indicated for the initial treatment of acute episodes of bronchospasm where rescue therapy is required for rapid response.

5.2 Hypersensitivity Reactions, Including Anaphylaxis

Hypersensitivity reactions including urticaria, angioedema, rash, bronchospasm, anaphylaxis, and oropharyngeal edema may occur after the administration of ATROVENT HFA. In clinical trials and postmarketing experience with ipratropium-containing products, hypersensitivity reactions such as skin rash, pruritus, angioedema of tongue, lips and face, urticaria (including giant urticaria), laryngospasm and anaphylactic reactions have been reported [see Adverse Reactions (6.1, 6.2)]. If such a reaction occurs, therapy with ATROVENT HFA should be stopped at once and alternative treatment should be considered [see Contraindications (4)].

5.3 Paradoxical Bronchospasm

ATROVENT HFA can produce paradoxical bronchospasm that can be life threatening. If this occurs, treatment with ATROVENT HFA should be stopped and other treatments considered.

5.4 Ocular Effects

ATROVENT HFA is an anticholinergic and its use may increase intraocular pressure. This may result in precipitation or worsening of narrow-angle glaucoma. Therefore, ATROVENT HFA should be used with caution in patients with narrow-angle glaucoma [see Drug Interactions (7.1)].

Patients should avoid spraying ATROVENT HFA into their eyes. If a patient sprays ATROVENT HFA into their eyes, they may cause eye pain or discomfort, temporary blurring of vision, mydriasis, visual halos or colored images in association with red eyes from conjunctival and corneal congestion. Advise patients to consult their physician immediately if any of these symptoms develop while using ATROVENT HFA Inhalation Aerosol.

5.5 Urinary Retention

ATROVENT HFA is an anticholinergic and may cause urinary retention. Therefore, caution is advised when administering ATROVENT HFA Inhalation Aerosol to patients with prostatic hyperplasia, or bladder-neck obstruction [see Drug Interactions (7.1)].

6 ADVERSE REACTIONS

The following adverse reactions are described, or described in greater detail, in other sections:

- Hypersensitivity Reactions, Including Anaphylaxis [see Contraindications (4) and Warnings and Precautions (5.2)]
- Paradoxical Bronchospasm [see Warnings and Precautions (5.3)]
- Ocular Effects [see Warnings and Precautions (5.4)]
- Urinary Retention [see Warnings and Precautions (5.5)]

Because clinical trials are conducted under widely varying conditions, adverse reaction rates observed in the clinical trials of a drug cannot be directly compared to rates in the clinical trials of another drug and may not reflect the rates observed in patients.

6.1 Clinical Trials Experience

The adverse reaction information concerning ATROVENT HFA is derived from two 12-week, double-blind, parallel-group studies and one 1-year open-label, parallel group study. These studies compared ATROVENT HFA Inhalation Aerosol, ATROVENT CFC Inhalation Aerosol, and placebo (in one study only) in 1,010 COPD patients. The following table lists the incidence of adverse reactions that occurred at a rate of greater than or equal to 3% in any ipratropium bromide group and greater than placebo in the 12-week study. The frequency of corresponding reactions in the 1-year open label study is included for comparison.

TABLE 1 Adverse Reactions (% Patients) in ATROVENT HFA Clinical Trials
 | Placebo-controlled 12-week Study 244.1405 and Active-controlled 12-week Study 244.1408 |  |  | Active-controlled 1-year Study 244.2453
 | ATROVENT HFA (N=243) % | ATROVENT CFC (N=183) % | Placebo (N=128) % | ATROVENT HFA (N=305) % | ATROVENT CFC (N=151) %
BODY AS A WHOLE - GENERAL DISORDERS
Back pain | 2 | 3 | 2 | 7 | 3
Headache | 6 | 9 | 8 | 7 | 5
Influenza-like symptoms | 4 | 2 | 2 | 8 | 5
CENTRAL & PERIPHERAL NERVOUS SYSTEM DISORDERS
Dizziness | 3 | 3 | 2 | 3 | 1
GASTROINTESTINAL SYSTEM DISORDERS
Dyspepsia | 1 | 3 | 1 | 5 | 3
Mouth dry | 4 | 2 | 2 | 2 | 3
Nausea | 4 | 1 | 2 | 4 | 4
RESPIRATORY SYSTEM DISORDERS
Bronchitis | 10 | 11 | 6 | 23 | 19
COPD exacerbation | 8 | 14 | 13 | 23 | 23
Dyspnea | 8 | 8 | 4 | 7 | 4
Sinusitis | 1 | 4 | 3 | 11 | 14
URINARY SYSTEM DISORDERS
Urinary tract infection | 2 | 3 | 1 | 10 | 8

Cough, rhinitis, and upper respiratory infection occurred in greater than or equal to 3% of patients in either ipratropium treatment group but not greater than placebo in the 12-week study.

In the one open-label controlled study in 456 COPD patients, the overall incidence of adverse events was also similar between ATROVENT HFA and ATROVENT CFC formulations.

Overall, in the above mentioned studies, 9.3% of the patients taking 42 mcg ATROVENT HFA and 8.7% of the patients taking 42 mcg ATROVENT CFC reported at least one adverse event that was considered by the investigator to be related to the study drug. The most common drug-related adverse events were dry mouth (1.6% of ATROVENT HFA and 0.9% of ATROVENT CFC patients), and taste perversion (bitter taste) (0.9% of ATROVENT HFA and 0.3% of ATROVENT CFC patients).

As an anticholinergic drug, cases of precipitation or worsening of narrow-angle glaucoma, glaucoma, halo vision, conjunctival hyperemia, corneal edema, mydriasis, acute eye pain, dry throat, hypotension, palpitations, urinary retention, tachycardia, constipation, bronchospasm, including paradoxical bronchospasm have been reported with the use of ATROVENT. Additional adverse reactions identified for ATROVENT seen in clinical trials include throat irritation, stomatitis, mouth edema, and vision blurred.

Allergic-type reactions such as skin rash, pruritus, angioedema including that of tongue, lips and face, urticaria (including giant urticaria), laryngospasm and anaphylactic reactions have been reported [see Warnings and Precautions (5.2)].

6.2 Postmarketing Experience

In a 5-year, placebo-controlled trial, hospitalizations for supraventricular tachycardia and/or atrial fibrillation occurred with an incidence rate of 0.5% in COPD patients receiving ATROVENT CFC.

In addition to the adverse reactions reported in the controlled clinical trials, adverse reactions have been identified during post-approval use of ATROVENT. Because these reactions are reported voluntarily from a population of uncertain size, it is not always possible to reliably estimate their frequency or establish a causal relationship to drug exposure.

Allergic-type reactions such as skin rash, angioedema including that of tongue, lips and face, urticaria (including giant urticaria), laryngospasm, and anaphylactic reactions have been reported, with positive rechallenge in some cases.

Additionally, urinary retention, mydriasis, gastrointestinal distress (diarrhea, nausea, vomiting), cough and bronchospasm, including paradoxical bronchospasm, hypersensitivity reactions, intraocular pressure increased, accommodation disorder, heart rate increased, pharyngeal edema, and gastrointestinal motility disorders have been reported during the postmarketing period with use of ATROVENT.

7 DRUG INTERACTIONS

ATROVENT HFA has been used concomitantly with other drugs, including sympathomimetic bronchodilators, methylxanthines, oral and inhaled steroids commonly used in the treatment of COPD. With the exception of albuterol, there are no formal studies fully evaluating the interaction effects of ATROVENT HFA and these drugs with respect to safety and effectiveness.

7.1 Anticholinergic Agents

There is potential for an additive interaction with concomitantly used anticholinergic medications. Therefore, avoid coadministration of ATROVENT HFA with other anticholinergic-containing drugs as this may lead to an increase in anticholinergic adverse effects [see Warnings and Precautions (5.4, 5.5)].

8 USE IN SPECIFIC POPULATIONS

8.1 Pregnancy

Risk Summary

Ipratropium is negligibly absorbed systemically following oral inhalation; therefore, maternal use is not expected to result in fetal exposure to the drug [see Clinical Pharmacology (12.3)]. There is limited experience with ipratropium bromide use in pregnant women. Published literature, including cohort studies, case control studies and case series, over several decades have not identified a drug associated risk of major birth defects, miscarriage or adverse maternal or fetal outcomes. Based on animal reproduction studies, no evidence of structural alterations was observed when ipratropium bromide was administered to pregnant mice, rats and rabbits during organogenesis at doses up to approximately 200, 40,000, and 10,000 times, respectively, the maximum recommended human daily inhalation dose (MRHDID) in adults (see Data).

The estimated background risk of major birth defects and miscarriage for the indicated population is unknown. All pregnancies have a background risk of birth defect, loss or other adverse outcomes. In the U.S. general population, the estimated background risk of major birth defects and miscarriage in clinically recognized pregnancies is 2% to 4% and 15% to 20%, respectively.

Data

Animal Data

In animal reproduction studies, oral and inhalation administration of ipratropium bromide to pregnant mice, rats and rabbits during the period of organogenesis did not show evidence of fetal structural alterations. The ipratropium bromide dose in oral studies in mice, rats, and rabbits was up to approximately 200, 40,000, and 10,000 times, respectively, the MRHDID in adults (on a mg/m^2 basis at maternal doses of 10, 1,000, and 125 mg/kg/day, respectively). The ipratropium bromide dose in inhalation studies in rats and rabbits was up to approximately 60 and 140 times, respectively, the MRHDID in adults (on a mg/m^2 basis at maternal doses of 1.5 and 1.8 mg/kg/day, respectively). Embryotoxicity was observed as increased resorption in rats at oral doses approximately 3,600 times the MRHDID in adults (on a mg/m^2 basis at maternal doses of 90 mg/kg/day and above). This effect is not considered relevant to human use due to the large doses at which it was observed and the difference in route of administration.

8.2 Lactation

Risk Summary

There are no data on the presence of ipratropium in either human or animal milk, the effects on the breastfed infant, or the effects on milk production. Although lipid-insoluble quaternary cations pass into breast milk, ipratropium concentrations in plasma after inhaled therapeutic doses are low, therefore, ipratropium levels in human breast milk are expected to be low [see Clinical Pharmacology (12.3)]. The developmental and health benefits of breastfeeding should be considered along with the mother's clinical need for ATROVENT HFA and any potential adverse effects on the breastfed child from ATROVENT HFA or from the underlying maternal condition.

8.4 Pediatric Use

Safety and effectiveness in the pediatric population have not been established.

8.5 Geriatric Use

In the pivotal 12-week study, both ATROVENT HFA and ATROVENT CFC formulations were equally effective in patients over 65 years of age and under 65 years of age. Of the total number of subjects in clinical studies of ATROVENT HFA, 57% were ≥65 years of age. No overall differences in safety or effectiveness were observed between these subjects and younger subjects.

10 OVERDOSAGE

Acute overdose by inhalation is unlikely since ipratropium bromide is not well absorbed systemically after inhalation or oral administration.

11 DESCRIPTION

The active ingredient in ATROVENT HFA is ipratropium bromide (monohydrate). It is an anticholinergic bronchodilator chemically described as 8-azoniabicyclo[3.2.1]octane, 3-(3-hydroxy-1-oxo-2-phenylpropoxy)-8-methyl-8-(1-methylethyl)-,bromide monohydrate, (3-endo, 8-syn)-: a synthetic quaternary ammonium compound, chemically related to atropine. The structural formula for ipratropium bromide is:

C20H30BrNO3∙H2O ipratropium bromide Mol. Wt. 430.4

Ipratropium bromide is a white to off-white crystalline substance, freely soluble in water and methanol, sparingly soluble in ethanol, and insoluble in lipophilic solvents such as ether, chloroform, and fluorocarbons.

ATROVENT HFA is a pressurized metered-dose aerosol unit for oral inhalation that contains a solution of ipratropium bromide. The 200 inhalation unit has a net weight of 12.9 grams. After priming, each actuation of the inhaler delivers 21 mcg of ipratropium bromide (monohydrate) from the valve in 56 mg of solution and delivers 17 mcg of ipratropium bromide (monohydrate) from the mouthpiece. The actual amount of drug delivered to the lung may depend on patient factors, such as the coordination between the actuation of the device and inspiration through the delivery system. The excipients are anhydrous citric acid, dehydrated alcohol, HFA-134a (1,1,1,2-tetrafluoroethane) as propellant, and sterile water for irrigation. This product does not contain chlorofluorocarbons (CFCs) as propellants.

ATROVENT HFA should be primed before using for the first time by releasing 2 test sprays into the air away from the face. In cases where the inhaler has not been used for more than 3 days, prime the inhaler again by releasing 2 test sprays into the air away from the face.

12 CLINICAL PHARMACOLOGY

12.1 Mechanism of Action

Ipratropium bromide is an anticholinergic (parasympatholytic) agent which, based on animal studies, appears to inhibit vagally-mediated reflexes by antagonizing the action of acetylcholine, the transmitter agent released at the neuromuscular junctions in the lung. Anticholinergics prevent the increases in intracellular concentration of Ca++ which is caused by interaction of acetylcholine with the muscarinic receptors on bronchial smooth muscle.

12.2 Pharmacodynamics

Cardiovascular effects

At recommended dosages, ipratropium bromide does not produce clinically significant changes in pulse rate or blood pressure.

Ocular effects

In studies without a positive control, ipratropium bromide did not alter pupil size, accommodation, or visual acuity.

Mucociliary clearance and respiratory secretions

Controlled clinical studies have demonstrated that ipratropium bromide does not alter either mucociliary clearance or the volume or viscosity of respiratory secretions.

12.3 Pharmacokinetics

Following administration by oral inhalation from a metered-dose inhaler, the majority of the delivered dose is deposited in the gastrointestinal tract and, to a lesser extent, in the lung, the intended site of action. Ipratropium bromide is a quaternary amine and hence is not readily absorbed into the systemic circulation either from the surface of the lung or from the gastrointestinal tract as confirmed by blood level and renal excretion studies.

The half-life of elimination is about 2 hours after inhalation or intravenous administration. Ipratropium bromide is minimally bound (0% to 9% in vitro) to plasma albumin and α1-acid glycoprotein. It is partially metabolized to inactive ester hydrolysis products. Following intravenous administration, approximately one-half of the dose is excreted unchanged in the urine.

A pharmacokinetic study with 29 chronic obstructive pulmonary disease (COPD) patients (48-79 years of age) demonstrated that mean peak plasma ipratropium concentrations of 59±20 pg/mL were obtained following a single administration of 4 inhalations of ATROVENT HFA (84 mcg). Plasma ipratropium concentrations declined to 24±15 pg/mL by six hours. When these patients were administered 4 inhalations QID (16 inhalations/day=336 mcg) for one week, the mean peak plasma ipratropium concentration increased to 82±39 pg/mL with a trough (6 hour) concentration of 28±12 pg/mL at steady state.

Specific Populations

Geriatric Patients

In the pharmacokinetic study with 29 COPD patients, a subset of 14 patients were >65 years of age. Mean peak plasma ipratropium concentrations of 56±24 pg/mL were obtained following a single administration of 4 inhalations (21 mcg/puff) of ATROVENT HFA (84 mcg). When these 14 patients were administered 4 inhalations four times a day (16 inhalations/day) for one week, the mean peak plasma ipratropium concentration only increased to 84±50 pg/mL indicating that the pharmacokinetic behavior of ipratropium bromide in the geriatric population is consistent with younger patients.

Renally Impaired Patients

The pharmacokinetics of ATROVENT HFA have not been studied in patients with renal insufficiency.

Hepatically Impaired Patients

The pharmacokinetics of ATROVENT HFA have not been studied in patients with hepatic insufficiency.

Drug-Drug Interaction

No specific pharmacokinetic studies were conducted to evaluate potential drug-drug interactions with other medications.

13 NONCLINICAL TOXICOLOGY

13.1 Carcinogenesis, Mutagenesis, Impairment of Fertility

Two-year oral carcinogenicity studies in rats and mice have revealed no carcinogenic activity at doses up to 6 mg/kg (approximately 240 and 120 times the maximum recommended human daily inhalation dose (MRHDID) in adults on a mg/m^2 basis, respectively). Results of various mutagenicity/clastogenicity studies (Ames test, mouse dominant lethal test, mouse micronucleus test and chromosome aberrations of bone marrow in Chinese hamsters) were negative.

Fertility of male or female rats at oral doses up to 50 mg/kg (approximately 2,000 times the MRHDID in adults on a mg/m^2 basis) was unaffected by ipratropium bromide administration. At an oral dose of 500 mg/kg (approximately 20,000 times the MRHDID in adults on a mg/m^2 basis), ipratropium bromide produced a decrease in the conception rate.

14 CLINICAL STUDIES

Conclusions regarding the efficacy of ATROVENT HFA were derived from two randomized, double-blind, controlled clinical studies. These studies enrolled males and females ages 40 years and older, with a history of COPD, a smoking history of >10 pack-years, an FEV1 <65% and an FEV1/FVC <70%.

One of the studies was a 12-week randomized, double-blind active, and placebo-controlled study in which 505 of the 507 randomized COPD patients were evaluated for the safety and efficacy of 42 mcg (n=124) and 84 mcg (n=126) ATROVENT HFA in comparison to 42 mcg (n=127) ATROVENT CFC and their respective placebos (HFA n=62, CFC n=66). Data for both placebo HFA and placebo CFC were combined in the evaluation.

Serial FEV1 (shown in Figure 1, below, as means adjusted for center and baseline effects on test day 1 and test day 85 (primary endpoint)) demonstrated that 1 dose (2 inhalations/21 mcg each) of ATROVENT HFA produced significantly greater improvement in pulmonary function than placebo. During the six hours immediately post-dose on day 1, the average hourly improvement in adjusted mean FEV1 was 0.148 liters for ATROVENT HFA (42 mcg) and 0.013 liters for placebo. The mean peak improvement in FEV1, relative to baseline, was 0.295 liters, compared to 0.138 liters for placebo. During the six hours immediately post-dose on day 85, the average hourly improvement in adjusted mean FEV1 was 0.141 liters for ATROVENT HFA (42 mcg) and 0.014 liters for placebo. The mean peak improvement in FEV1, relative to baseline, was 0.295 liters, compared to 0.140 liters for placebo.

ATROVENT HFA (42 mcg) was shown to be clinically comparable to ATROVENT CFC (42 mcg).

Figure 1 Day 1 and Day 85 (Primary Endpoint) Results

In this study, both ATROVENT HFA and ATROVENT CFC formulations were equally effective in patients over 65 years of age and under 65 years of age.

The median time to improvement in pulmonary function (FEV1 increase of 15% or more) was within approximately 15 minutes, reached a peak in 1 to 2 hours, and persisted for 2 to 4 hours in the majority of the patients. Improvements in Forced Vital Capacity (FVC) were also demonstrated.

The other study was a 12-week, randomized, double-blind, active-controlled clinical study in 174 adults with COPD, in which ATROVENT HFA 42 mcg (n=118) was compared to ATROVENT CFC 42 mcg (n=56). Safety and efficacy of HFA and CFC formulations were shown to be comparable.

The bronchodilatory efficacy and comparability of ATROVENT HFA vs ATROVENT CFC were also studied in a one-year open-label safety and efficacy study in 456 COPD patients. The safety and efficacy of HFA and CFC formulations were shown to be comparable.

16 HOW SUPPLIED/STORAGE AND HANDLING

ATROVENT HFA is supplied in a pressurized stainless steel canister as a metered-dose inhaler with a white mouthpiece that has a clear, colorless sleeve and a green protective cap (NDC 0597-0087-17). The mouthpiece has an actuation indicator visible through a small window. The indicator typically moves during every 5 to 7 actuations. It displays the approximate number of actuations remaining in increments of 20, starting at "200" and decreasing until it reaches "0".

The ATROVENT HFA canister is to be used only with the accompanying ATROVENT HFA mouthpiece. This mouthpiece should not be used with other aerosol medications. Similarly, the canister should not be used with other mouthpieces. After priming, each actuation of ATROVENT HFA delivers 21 mcg of ipratropium bromide (monohydrate) from the valve and 17 mcg from the mouthpiece. Each canister has a net weight of 12.9 grams and provides sufficient medication for 200 actuations. The inhaler should be discarded after the labeled number of actuations has been used when the indicator displays "0". The amount of medication in each actuation cannot be assured after this point, even though the canister is not completely empty.

Storage

Store at 20°C to 25°C (68°F to 77°F); excursions permitted to 15°C to 30°C (59°F to 86°F) [see USP Controlled Room Temperature]. For optimal results, the canister should be at room temperature before use.

Contents Under Pressure: Do not puncture. Do not use or store near heat or open flame. Exposure to temperatures above 120°F may cause bursting. Never throw the inhaler into a fire or incinerator.

Keep out of reach of children. Avoid spraying in eyes.

17 PATIENT COUNSELING INFORMATION

Advise the patient to read the FDA-approved patient labeling (Instructions for Use).

Appropriate and safe use of ATROVENT HFA includes providing the patient with the information listed below and an understanding of the way it should be administered.

Advise patients that ATROVENT HFA is a bronchodilator for the maintenance treatment of bronchospasm associated with COPD and is not indicated for the initial treatment of acute episodes of bronchospasm where rescue therapy is required for rapid response.

Hypersensitivity Reactions

Inform patients that hypersensitivity reactions, including urticaria, angioedema, rash, bronchospasm, anaphylaxis, and oropharyngeal edema, may occur after the administration of ATROVENT HFA. Advise patients to immediately discontinue ATROVENT HFA and consult a physician [see Warnings and Precautions (5.2)].

Paradoxical Bronchospasm

Inform patients that ATROVENT HFA can produce paradoxical bronchospasm that can be life-threatening. If paradoxical bronchospasm occurs, patients should discontinue using ATROVENT HFA.

Ocular Effects

Caution patients to avoid spraying the aerosol into their eyes and be advised that this may result in precipitation or worsening of narrow-angle glaucoma, mydriasis, increased intraocular pressure, acute eye pain or discomfort, temporary blurring of vision, visual halos or colored images in association with red eyes from conjunctival and corneal congestion. Patients should also be advised that should any combination of these symptoms develop, they should consult their physician immediately.

Since dizziness, accommodation disorder, mydriasis, and blurred vision may occur with use of ATROVENT HFA, patients should be cautioned about engaging in activities requiring balance and visual acuity such as driving a car or operating appliances or machinery.

Urinary Retention

Inform patients that ATROVENT HFA may cause urinary retention and should be advised to consult their physicians if they experience difficulty with urination.

Frequency of Use

The action of ATROVENT HFA should last 2 to 4 hours. Advise patients not to increase the dose or frequency of ATROVENT HFA without patients consulting their physician. Advise patients to seek immediate medical attention if treatment with ATROVENT HFA becomes less effective for symptomatic relief, their symptoms become worse, and/or patients need to use the product more frequently than usual.

Concomitant Drug Use

Advise patients on the use of ATROVENT HFA in relation to other inhaled drugs [see Drug Interactions (7.1)].

Use Only as Prescribed

Remind patients that ATROVENT HFA should be used consistently as prescribed throughout the course of therapy.

Preparation for Use and Priming

Instruct patients that priming ATROVENT HFA is essential to ensure appropriate content of the medication in each actuation. Patients do not have to shake the ATROVENT HFA canister before use.

Distributed by:
Boehringer Ingelheim Pharmaceuticals, Inc.
Ridgefield, CT 06877 USA

Licensed from:
Boehringer Ingelheim International GmbH

ATROVENT® is a registered trademark of and used under license from Boehringer Ingelheim International GmbH

Copyright © 2024 Boehringer Ingelheim International GmbH
ALL RIGHTS RESERVED

COL9554BA022025
SPL9556D

INSTRUCTIONS FOR USE

ATROVENT® HFA

(ipratropium bromide HFA)
Inhalation Aerosol, for oral inhalation use

Read this Instructions for Use before using your ATROVENT HFA and each time you get a refill. There may be new information. This leaflet does not take the place of talking with your healthcare provider about your medical condition or your treatment.

Use ATROVENT HFA exactly as your healthcare provider tells you to. Do not change your dose or how often you use ATROVENT HFA without talking with your healthcare provider.

Tell your doctor about all the medicines you take. ATROVENT HFA may affect the way some other medicines work and some other medicines may affect the way ATROVENT HFA works.

Important information about using ATROVENT HFA

- You do not have to shake ATROVENT HFA before using it.
- ATROVENT HFA should be "primed" 2 times before you use the first dose of a new ATROVENT HFA inhaler or when the inhaler has not been used for more than 3 days.
  - To prime, push the canister against the mouthpiece (see Figure 1), allowing the medicine to spray into the air.
  - Do not spray the medicine into your eyes while priming ATROVENT HFA.

Inhaler Description

ATROVENT HFA Inhalation Aerosol (Figure 1) consists of a metal canister containing the medicine and a mouthpiece that releases the medicine from the canister. The mouthpiece includes a clear colorless sleeve, a white plastic portion and a green protective dust cap.

The inhaler comes with a dose indicator you can see through a small window on the plastic mouthpiece (see Figure 1). A new inhaler first shows "200" in the dose indicator window. The dose indicator will show the approximate number of actuations (sprays) of medicine remaining in the inhaler. As you use the inhaler, the dose indicator will typically rotate during every 5 to 7 actuations (sprays) towards the next decreasing number (see Figure 2).

Figure 1

Figure 2

Instructions for Use:

1. Insert the metal canister into the clear end of the mouthpiece (see Figure 1). Make sure the canister is fully and firmly inserted into the mouthpiece.
  - The ATROVENT HFA canister is to be used only with the ATROVENT HFA mouthpiece.
  - Do not use the ATROVENT HFA mouthpiece with other inhaled medicines.
2. Remove the green protective dust cap. If the cap is not on the mouthpiece, make sure there is nothing in the mouthpiece before use. For best results, the canister should be at room temperature before use.
3. Breathe out (exhale) deeply through your mouth. Hold the inhaler upright (see Figure 3). Put the mouthpiece in your mouth and close your lips.
  - Keep your eyes closed so that no medicine will be sprayed into your eyes. If sprayed into the eyes, ATROVENT HFA can cause blurry vision and other vision abnormalities, eye pain or discomfort, dilated pupils, or narrow-angle glaucoma or worsening of this condition. If any combination of these symptoms develops, you should consult your physician immediately.

Figure 3

4. Breathe in (inhale) slowly through your mouth and at the same time spray the ATROVENT HFA into your mouth.
  - To spray ATROVENT HFA firmly press the canister against the mouthpiece 1 time (see Figure 4). Keep breathing in deeply.

Figure 4

5. Hold your breath for ten seconds and then take the mouthpiece out of your mouth and breathe out slowly (see Figure 5).

Figure 5

6. Wait at least 15 seconds and repeat steps 3 to 5 again.
7. Replace the green protective dust cap after use.
8. Keep the mouthpiece clean. At least once a week, wash the mouthpiece, shake it to remove excess water and let it air dry all the way (see Mouthpiece Cleaning Instructions).

Mouthpiece Cleaning Instructions:

Step A. Remove and set aside the canister and dust cap from the mouthpiece (see Figure 1).

Step B. Wash the mouthpiece through the top and bottom with warm running water for at least 30 seconds (see Figure 6). Do not use anything other than water to wash the mouthpiece.

Figure 6

Step C. Dry the mouthpiece by shaking off the excess water and allow it to air dry all the way.

Step D. When the mouthpiece is dry, replace the canister. Make sure the canister is fully and firmly inserted into the mouthpiece.

Step E. Replace the green protective dust cap.

If little or no medicine comes out of the mouthpiece, wash the mouthpiece as described in Steps A to E under the "Mouthpiece Cleaning Instructions".

9. When to get a new ATROVENT HFA inhaler.
  There are approximately 40 actuations (sprays) left when the dose indicator displays "40," where the background changes from green to red (see Figure 7a). This is when you need to refill your prescription or ask your doctor if you need another prescription for ATROVENT HFA inhalation aerosol.
  The background color will be all red when the indicator approaches 20. The indicator will stop moving at "0". Discard the inhaler once the dose indicator displays "0" (see Figure 7b). Even though the canister may not be empty, you cannot be sure of the amount of medicine in each actuation (spray) once the dose indicator displays "0".

Figure 7a

Figure 7b

This product does not contain any chlorofluorocarbon (CFC) propellants.

The contents of ATROVENT HFA are under pressure. Do not puncture the canister. Do not use or store near heat or open flame. Exposure to temperatures above 120°F may cause bursting. Never throw the container into a fire or incinerator.

Keep ATROVENT HFA and all medicines out of the reach of children.

Store ATROVENT HFA at room temperature 68°F to 77°F (20°C to 25°C). Short-term exposure to higher or lower temperatures [from 59°F (15°C) to 86°F (30°C)] is acceptable.

For more information about ATROVENT HFA including current prescribing information and Instructions for Use, go to www.atrovent.com, scan the code, or call Boehringer Ingelheim Pharmaceuticals, Inc. at 1-800-542-6257.

This Instructions for Use has been approved by the U.S. Food and Drug Administration.

Distributed by:
Boehringer Ingelheim Pharmaceuticals, Inc.
Ridgefield, CT 06877 USA

Licensed from:
Boehringer Ingelheim International GmbH

ATROVENT® is a registered trademark of and used under license from Boehringer Ingelheim International GmbH

Copyright © 2024 Boehringer Ingelheim International GmbH
ALL RIGHTS RESERVED

COL9554BA022025

Revised: December 2024

PRINCIPAL DISPLAY PANEL - 17 mcg Canister Carton

NDC 0597-0087-17

Atrovent® HFA
(ipratropium bromide HFA
inhalation aerosol)

17 mcg/actuation

Each actuation delivers 17 mcg ipratropium
bromide (monohydrate) from the mouthpiece.

Rx only

with Dose Indicator

12.9 grams/200 metered actuations

Boehringer
Ingelheim